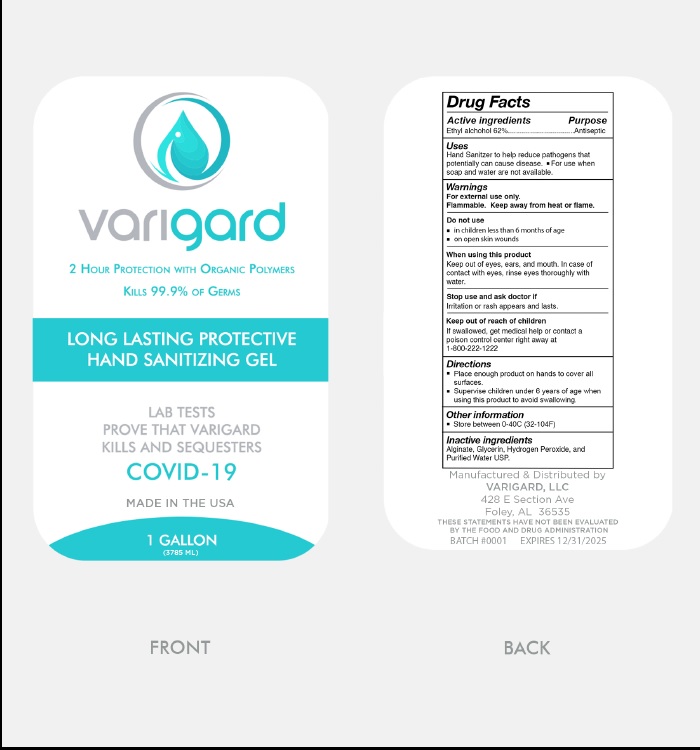 DRUG LABEL: Varigard Hand Sanitizer
NDC: 80787-001 | Form: GEL
Manufacturer: VARIGARD, LLC
Category: otc | Type: HUMAN OTC DRUG LABEL
Date: 20221222

ACTIVE INGREDIENTS: ALCOHOL 62 mL/100 mL
INACTIVE INGREDIENTS: GLYCERIN; HYDROGEN PEROXIDE; WATER

Active Ingredient

Ethyl Alcohol 62% v/v.

Purpose

Antiseptic

Use

- Hand Sanitizer to help reduce bacteria that potentially can cause disease.
- For use when soap and water are not available.

Warnings

For external use only.

Flammable. Keep away from heat or flame

Do not use

- in children less than 2 months of age
- on open skin wounds

When using this product keep out of eyes, ears, and mouth. In case of contact with eyes, rinse eyes thoroughly with water.

Stop use and ask a doctor if irritation or rash appears and lasts.

Keep out of reach of children. If swallowed, get medical help or contact a Poison Control Center right away at 1-800-222-1222

Directions

- Place enough product on hands to cover all surfaces.
- Supervise children under 6 years of age when using this product to avoid swallowing.

Other information

- Store between 0-40ºC (32-104ºF)

Inactive ingredients

Alginate, Glycerin, Hydrogen Peroxide, Purified Water USP